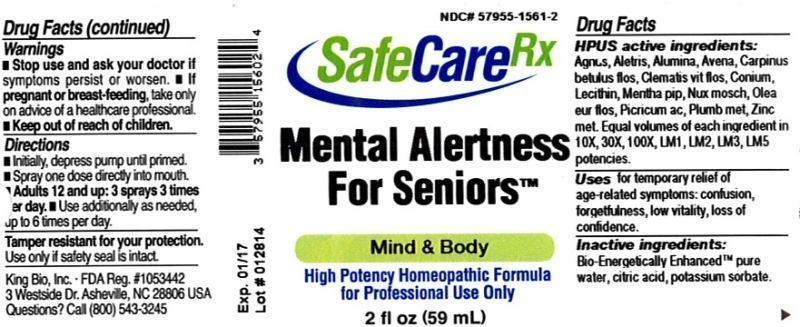 DRUG LABEL: Mental Alertness For Seniors
NDC: 57955-1561 | Form: LIQUID
Manufacturer: King Bio Inc.
Category: homeopathic | Type: HUMAN OTC DRUG LABEL
Date: 20140604

ACTIVE INGREDIENTS: CHASTE TREE 10 [hp_X]/59 mL; ALETRIS FARINOSA ROOT 10 [hp_X]/59 mL; ALUMINUM OXIDE 10 [hp_X]/59 mL; AVENA SATIVA FLOWERING TOP 10 [hp_X]/59 mL; CARPINUS BETULUS FLOWERING TOP 10 [hp_X]/59 mL; CLEMATIS VITALBA FLOWER 10 [hp_X]/59 mL; CONIUM MACULATUM FLOWERING TOP 10 [hp_X]/59 mL; EGG PHOSPHOLIPIDS 10 [hp_X]/59 mL; MENTHA PIPERITA 10 [hp_X]/59 mL; NUTMEG 10 [hp_X]/59 mL; OLEA EUROPAEA FLOWER 10 [hp_X]/59 mL; PICRIC ACID 10 [hp_X]/59 mL; LEAD 10 [hp_X]/59 mL; ZINC 10 [hp_X]/59 mL
INACTIVE INGREDIENTS: WATER; CITRIC ACID MONOHYDRATE; POTASSIUM SORBATE

Mental Alertness For Seniors™

ACTIVE INGREDIENT

Drug Facts__________________________________________________________________________________________________________

HPUS active ingredients: Agnus castus, Aletris farinosa, Alumina, Avena sativa, Carpinus betulus, flos, Clematis vitalba, flos, Conium maculatum, Lecithin, Mentha piperita, Nux moschata, Olea europaea, flos, Picricum acidum, Plumbum metallicum, Zincum metallicum. Equal volumes of each ingredient in 10X, 30X, 100X, LM1, LM2, LM3, LM5 potencies.

INDICATIONS AND USAGE

Uses for temporary relief of age-related symptoms: confusion, forgetfulness, low vitality, loss of confidence.

Inactive Ingredients:

Bio-Energetically Enhanced™ pure water, citric acid and potassium sorbate.

Warnings

- Stop use and ask your doctor if symptoms persist or worsen.
- If pregnant or breast-feeding, take only on advice of a healthcare professional.

- Keep out of reach of children.

Directions

- Initially, depress pump until primed.
- Spray one dose directly into mouth.
- Adults 12 and up: 3 sprays 3 times per day.
- Use additionally as needed, up to 6 times per day.

OTHER SAFETY INFORMATION

Tamper resistant for your protection. Use only if safety seal is intact.

PURPOSE

Uses for temporary relief of age-related symptoms:

- confusion
- forgetfulness
- low vitality
- loss of confidence